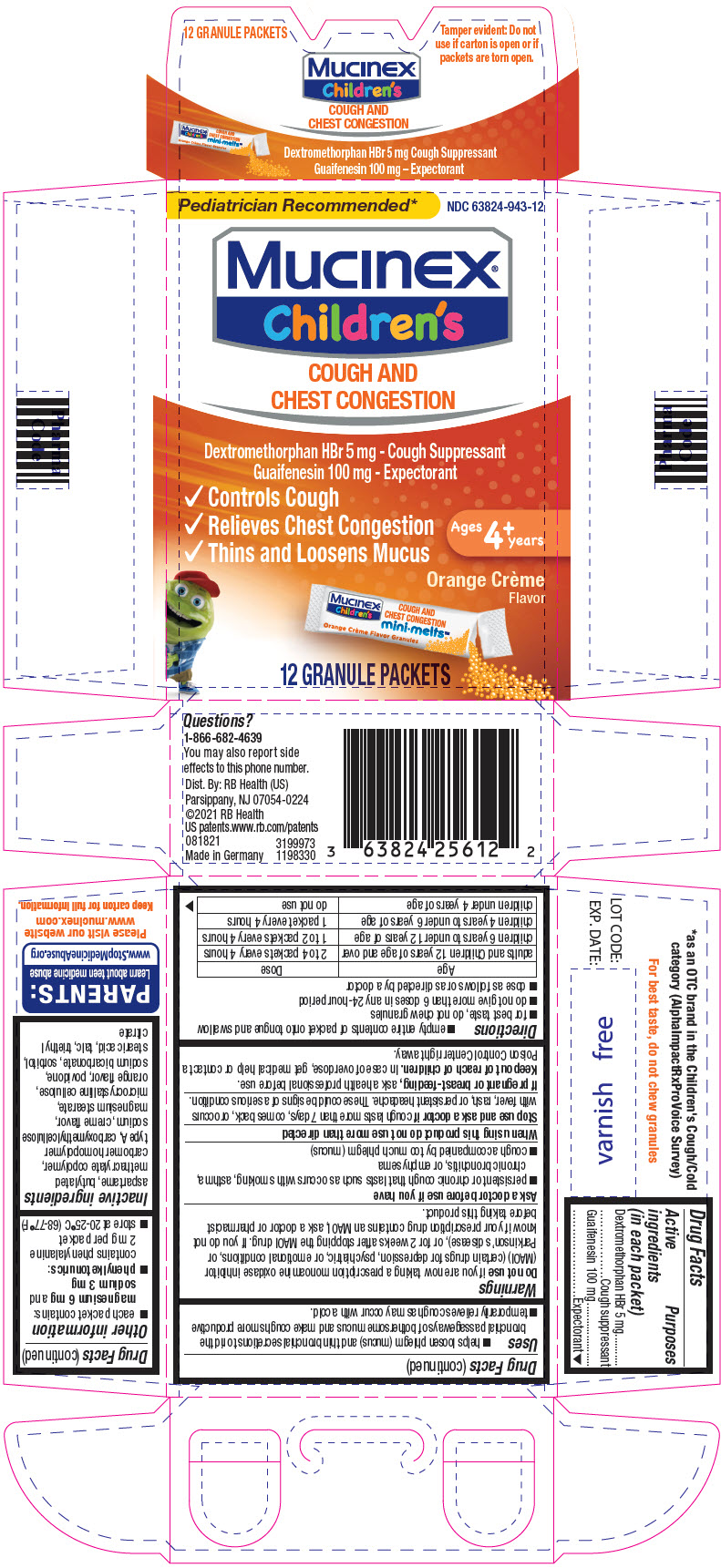 DRUG LABEL: Mucinex Childrens
NDC: 63824-943 | Form: GRANULE
Manufacturer: RB Health (US) LLC
Category: otc | Type: HUMAN OTC DRUG LABEL
Date: 20241218

ACTIVE INGREDIENTS: DEXTROMETHORPHAN HYDROBROMIDE 5 mg/1 1; GUAIFENESIN 100 mg/1 1
INACTIVE INGREDIENTS: ASPARTAME; CARBOMER HOMOPOLYMER TYPE A (ALLYL PENTAERYTHRITOL CROSSLINKED); CARBOXYMETHYLCELLULOSE SODIUM, UNSPECIFIED; MAGNESIUM STEARATE; MICROCRYSTALLINE CELLULOSE; POVIDONE, UNSPECIFIED; SODIUM BICARBONATE; SORBITOL; STEARIC ACID; TALC; TRIETHYL CITRATE

Mucinex® Children's
Cough & Chest Congestion Mini-Melts Orange Crème

Drug Facts

ACTIVE INGREDIENT

PURPOSE

Active ingredients (in each packet) | Purposes
Dextromethorphan HBr 5 mg | Cough suppressant
Guaifenesin 100 mg | Expectorant

Uses

- helps loosen phlegm (mucus) and thin bronchial secretions to rid the bronchial passageways of bothersome mucus and make coughs more productive
- temporarily relieves cough as may occur with a cold.

Warnings

DO NOT USE

Do not useif you are now taking a prescription monoamine oxidase inhibitor (MAOI) (certain drugs for depression, psychiatric, or emotional conditions, or Parkinson's disease), or for 2 weeks after stopping the MAOI drug. If you do not know if your prescription drug contains an MAOI, ask a doctor or pharmacist before taking this product.

Ask a doctor before use if you have

- persistent or chronic cough that lasts such as occurs with smoking, asthma, chronic bronchitis, or emphysema
- cough accompanied by too much phlegm (mucus)

When using this product do not use more than directed

Stop use and ask a doctor ifcough lasts more than 7 days, comes back, or occurs with fever, rash, or persistent headache. These could be signs of a serious condition.

PREGNANCY OR BREAST FEEDING

If pregnant or breast-feeding,ask a health professional before use.

Keep out of reach of children.In case of overdose, get medical help or contact a Poison Control Center right away.

Directions

- empty entire contents of packet onto tongue and swallow
- for best taste, do not chew granules
- do not give more than 6 doses in any 24-hour period
- dose as follows or as directed by a doctor

Age | Dose
adults and Children 12 years of age and over | 2 to 4 packets every 4 hours
children 6 years to under 12 years of age | 1 to 2 packets every 4 hours
children 4 years to under 6 years of age | 1 packet every 4 hours
children under 4 years of age | do not use

Other information

- each packet contains: magnesium 6 mgand sodium 3 mg
- phenylketonurics: contains phenylalanine 2 mg per packet
- store at 20-25°C (68-77°F)

Inactive ingredients

aspartame, butylated methacrylate copolymer, carbomer homopolymer type A, carboxymethylcellulose sodium, creme flavor, magnesium stearate, microcrystalline cellulose, orange flavor, povidone, sodium bicarbonate, sorbitol, stearic acid, talc, triethyl citrate

Questions?

1-866-682-4639

You may also report side effects to this phone number.

Dist. By: RB Health (US)
Parsippany, NJ 07054-0224

Made in Germany

PRINCIPAL DISPLAY PANEL - 12 Packet Carton

Pediatrician Recommended*

NDC 63824-943-12

Mucinex®
children's

COUGH AND
CHEST CONGESTION

Dextromethorphan HBr 5 mg - Cough Suppressant
Guaifenesin 100 mg - Expectorant

- Controls Cough
- Relieves Chest Congestion
- Thins and Loosens Mucus

Ages
4^+years

Orange Crème
Flavor

12 GRANULE PACKETS